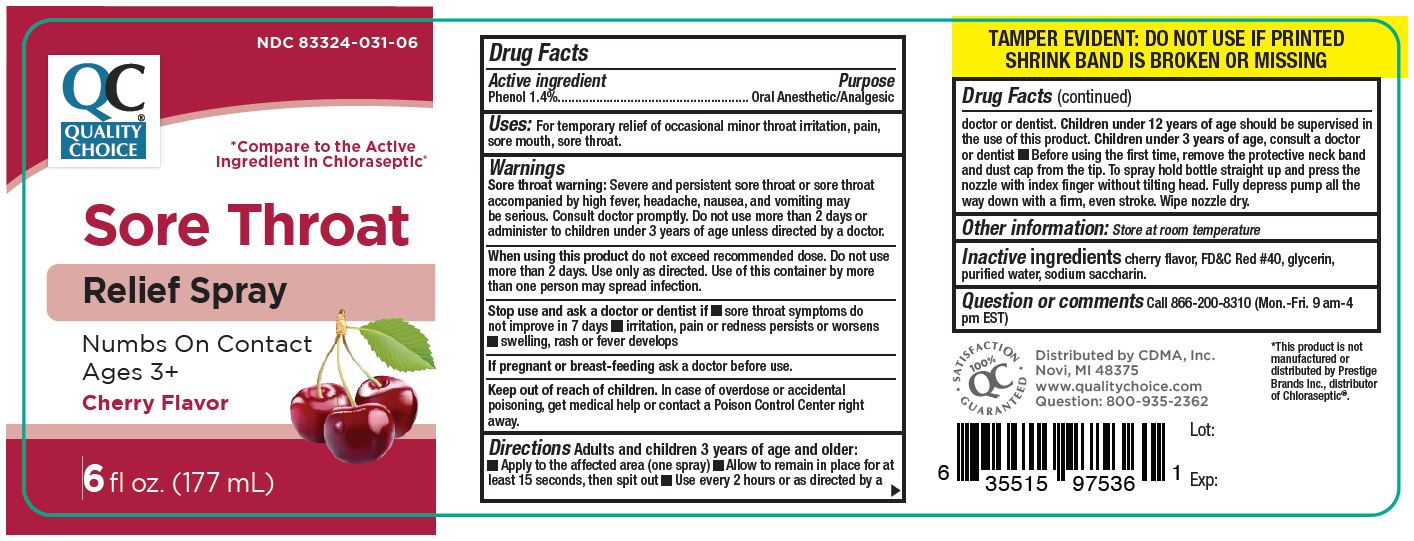 DRUG LABEL: PHENOL
NDC: 83324-031 | Form: SPRAY
Manufacturer: CHAIN DRUG MARKETING ASSOCIATION INC.
Category: otc | Type: HUMAN OTC DRUG LABEL
Date: 20241213

ACTIVE INGREDIENTS: PHENOL 14 mg/100 mL
INACTIVE INGREDIENTS: FD&C RED NO. 40; GLYCERIN; SODIUM SACCHARIN; WATER

Sore Throat
Relief Spray

Active Ingredient Purpose

Phenol 1.4%............. Oral Anesthetic/Analgesic

PURPOSE

Sore Throat Relief

Uses

- For temporary relief of occasional minor throat irritation, pain, sore mouth, sore throat.

Warnings

WHEN USING

Sore throat waring: Severe and persistent sore throat or sore throat accompanied by high fever, headache, nausea, and vomiting may be serious. Consult doctor promptly. Do not use more than 2 days or administer to children under 3 years of age unless directed by a doctor.

Whan using this product do not exceed recommended dose. Do not use more than 2 days. Use only as directed. Use of this container by more
than one person may spread infection.

Stop use and ask a doctor or dentist if

- sore throat symptoms do not improve in 7 days
- irritation, pain or redness persists or worsens
- swelling, rash or fever develops

If pregnant or breast-feeding ask a doctor before use.

Keep out of reach of children. In case of overdose or accidental poisoning, get medical help or contact a Poison Control Center right away.

Directions

Adults and children 3 years of age and older.

- Apply to the affected area (one spray)
- Allow to remain in place for at least 15 seconds, then spit out
- Use every 2 hours or as directed by a doctor or dentist. Children under 12 years of age should be supervised in the use of this product. Children under 3 years of age, consult a doctor or dentist
- Before using the first time, remove the protective neck band and dust cap from the tip. To spray hold bottle straight up and press the
  nozzle with index finger without tilting head. Fully depress pump all the way down with a firm, even stroke. Wipe nozzle dry.

Other information

- Store at room temperature

Inactive ingredients

cherry flavor, FD&C Red #40, glycerin, purified water, sodium saccharin.

- Tamper Evident: Do not use if printed shrink band is broken or missing.
- This product is not manufactured or distributed by Prestige Brands Inc., distributor of Chloraseptic.

Questions or comments?
call 866-200-8310 (Mon-Fri. 9 am-5 pm EST)

Distributed by C.D.M.A Inc.
Novi, MI 48375
www.qualitychoice.com
Question: 800-935-2362

PRINCIPAL DISPLAY PANEL

NDC-83324-031-06